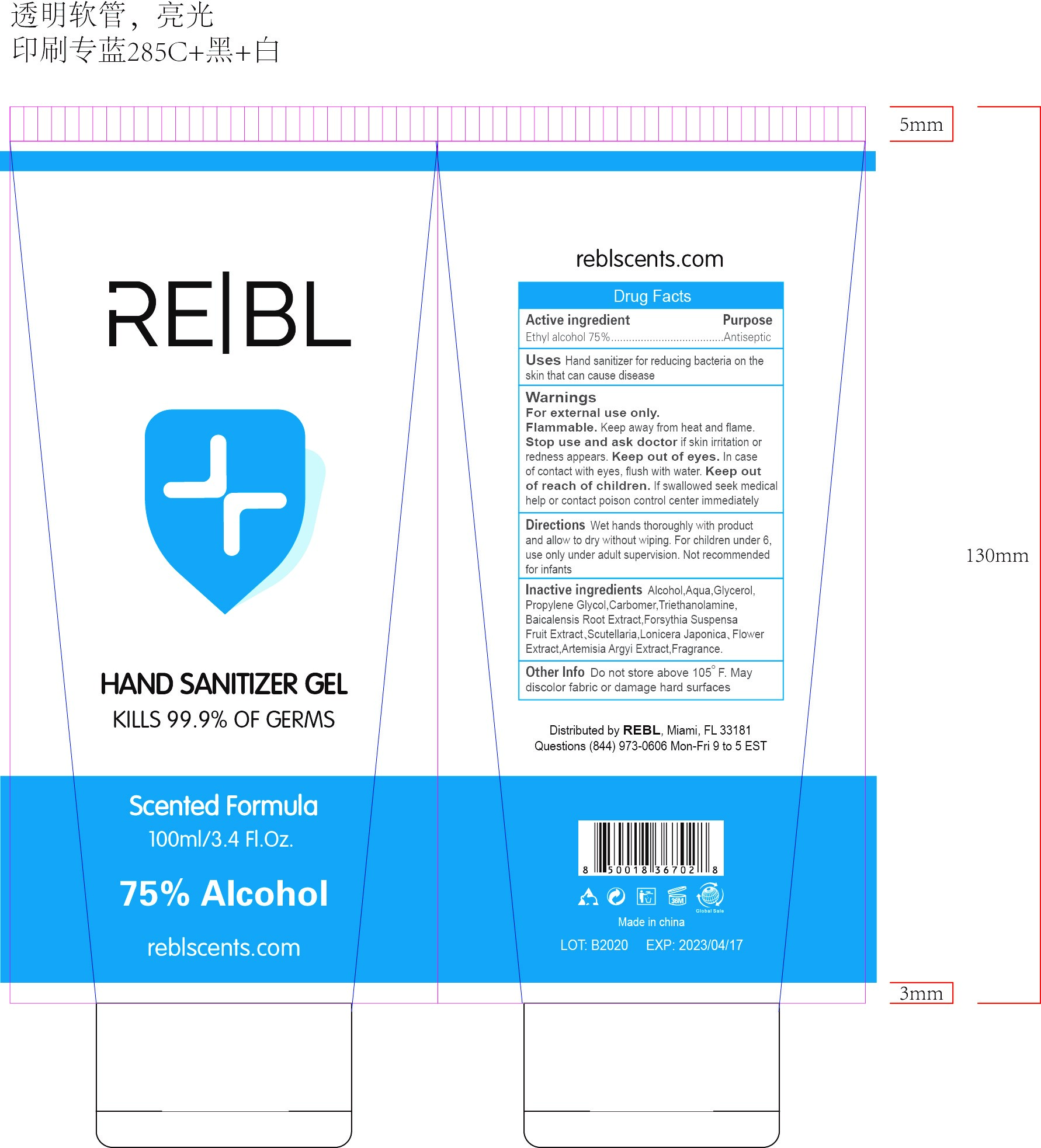 DRUG LABEL: Hand Sanitizer
NDC: 78049-001 | Form: GEL
Manufacturer: GUANG DONG MEIBAO COSMETICS CO.,LTD
Category: otc | Type: HUMAN OTC DRUG LABEL
Date: 20200520

ACTIVE INGREDIENTS: ALCOHOL 75 mL/100 mL
INACTIVE INGREDIENTS: GLYCERIN; WATER

hand sanitizer gel

Active Ingredient(s)

Ethyl Alcohol 75% . Purpose: Antiseptic

Purpose

Antiseptic, Hand Sanitizer

Use

Hand Sanitizer for reducing bacteria on the skin that can cause disease.

Warnings

For external use only. Flammable. Keep away from heat or flame

Stop use and ask a doctor if irritation or or redness appear

Keep out of reach of children. If swallowed, get medical help or contact a Poison Control Center right away.

Directions

wet hands thoroughly with product and allow to dry without wiping.for children under 6.use only under adult supervision not recommended for infants

Other information

Do not store above 105℉. may discolor fabric or damage hard surface

Inactive ingredients

glycerol, water

Package Label - Principal Display Panel

100 mL NDC: 78049-001-01